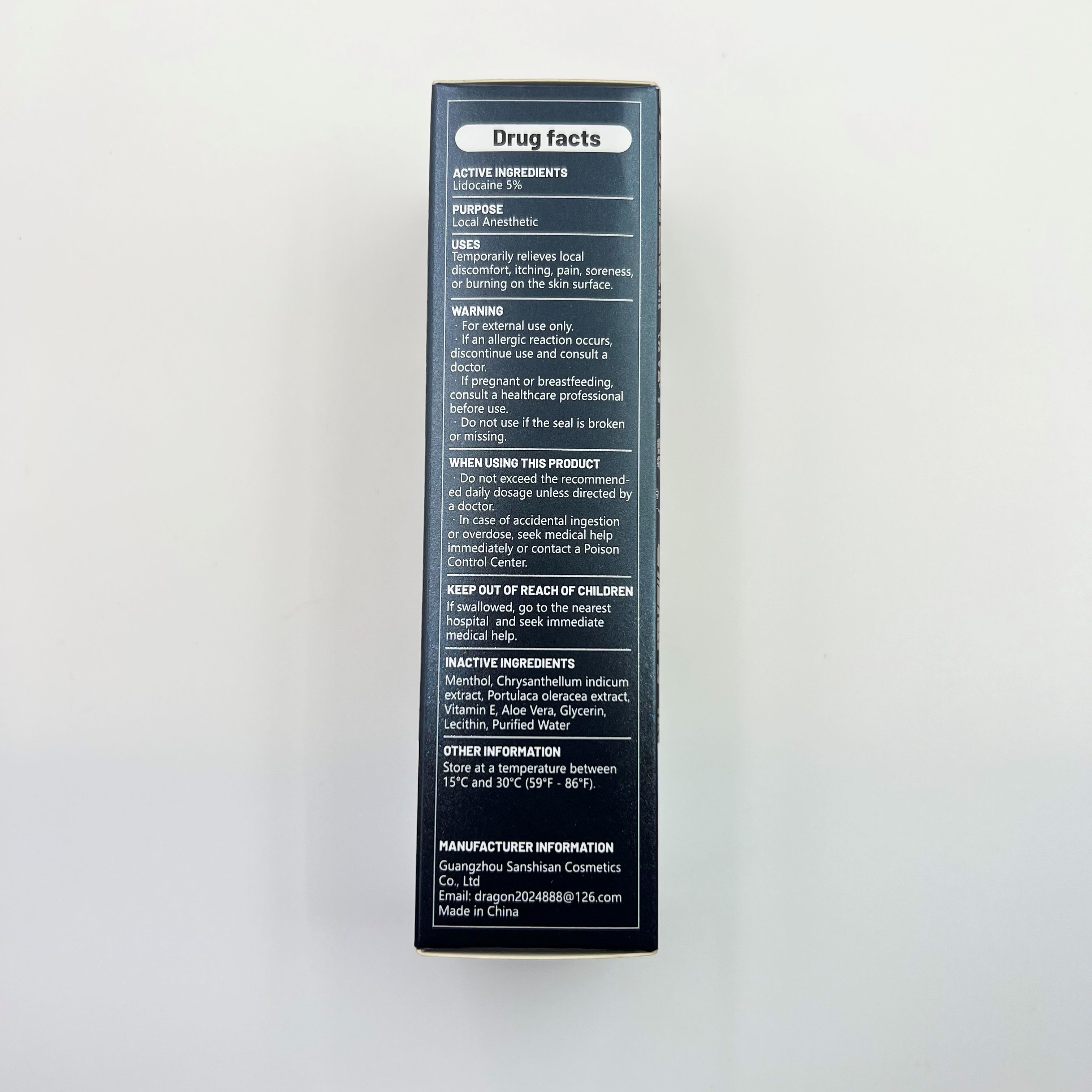 DRUG LABEL: Tattoo numbing
NDC: 85342-002 | Form: CREAM
Manufacturer: Guangzhou Sanshisan Cosmetics Co., Ltd.
Category: otc | Type: HUMAN OTC DRUG LABEL
Date: 20250421

ACTIVE INGREDIENTS: LIDOCAINE 3 g/60 g
INACTIVE INGREDIENTS: MENTHOL; PURSLANE; CHRYSANTHELLUM INDICUM TOP; TOCOPHEROL; AQUA; LECITHIN, SOYBEAN; GLYCERIN; ALOE

ACTIVE INGREDIENT

Lidocaine:5%

INACTIVE INGREDIENT

Menthol
Chrysanthellum indicum extract
Portulaca oleracea extract
Vitamin E
Aloe Vera
Glycerin
Lecithin
Purified Water

PURPOSE

Local Anesthetic

WARNING
For external use only.lf an allergic reaction occursdiscontinue use and consult adoctor.
lf pregnant or breastfeeding,consult a healthcare professionalbefore use.
Do not use if the seal is brokenor missing

Do not use if the seal is brokenor missing

DO NOT USE

lf pregnant or breastfeeding,consult a healthcare professionalbefore use.

KEEP OUT OF REACHOF CHIDREN

If swallowed, go to the nearesthospital and seek immediatemedical help.

INDICATIONS AND USAGE

USESTemporarily relieves localdiscomfort, itching, pain, soreness,or burning on the skin surface.

WHEN USING

WHEN USING THIS PRODUCTDo not exceed the recommended daily dosage unless directed bya doctor.
In case of accidental ingestionor overdose, seek medical helpimmediately or contact a PoisonControl Center.

DOSAGE AND ADMINISTRATION

to an appropriate extent for product